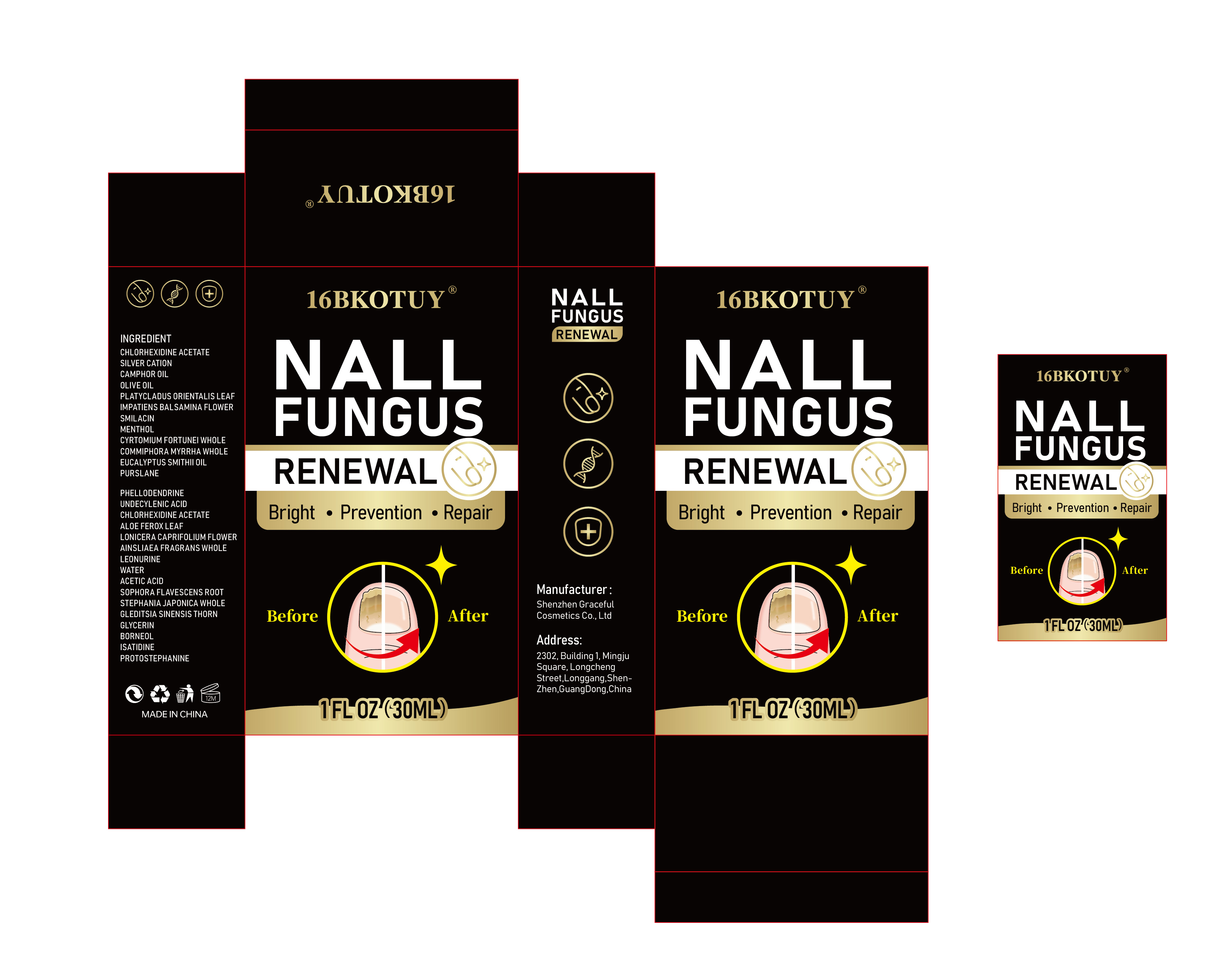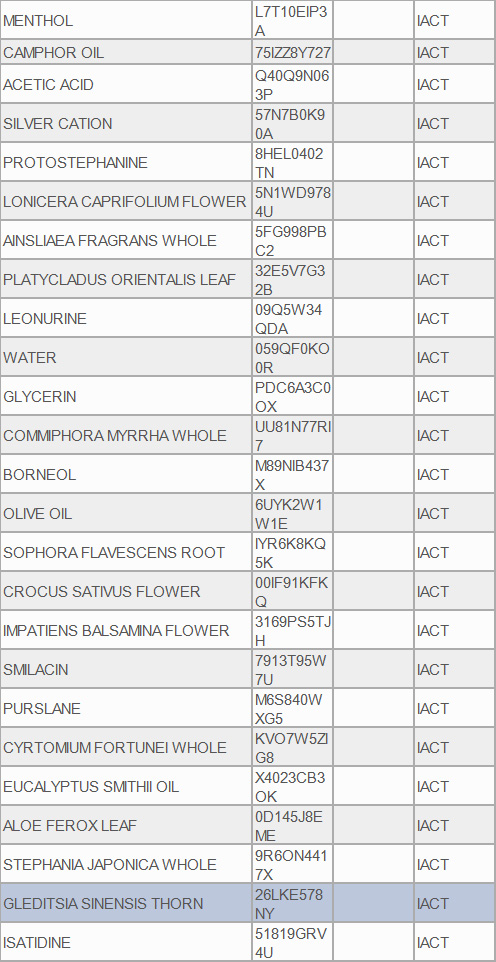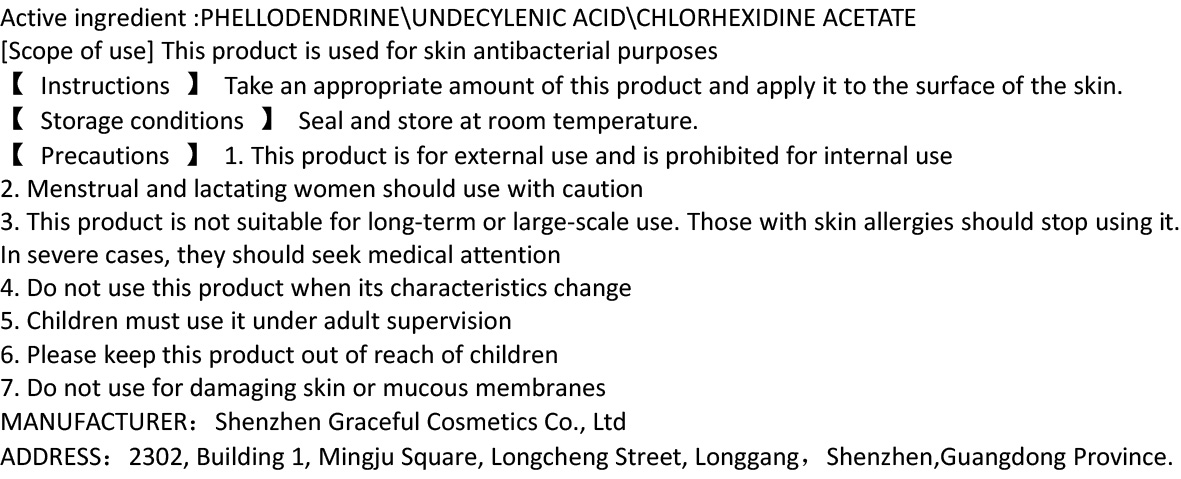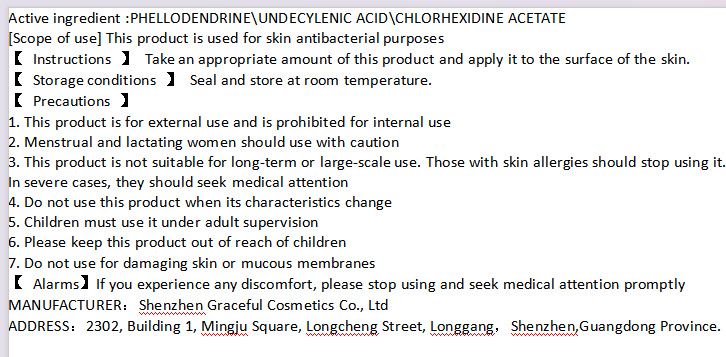 DRUG LABEL: 16BKOUTY NALL FUNGUS RENEWAL
NDC: 84422-101 | Form: LIQUID
Manufacturer: Shenzhen Graceful Cosmetics Co., Ltd
Category: otc | Type: HUMAN OTC DRUG LABEL
Date: 20240727

ACTIVE INGREDIENTS: PHELLODENDRINE 1 g/100 mL; UNDECYLENIC ACID 10 g/100 mL
INACTIVE INGREDIENTS: WATER; MENTHOL; CAMPHOR OIL; ACETIC ACID; SILVER CATION; PROTOSTEPHANINE; LONICERA CAPRIFOLIUM FLOWER; AINSLIAEA FRAGRANS WHOLE; PLATYCLADUS ORIENTALIS LEAF; CHLORHEXIDINE ACETATE 0.2 g/100 mL; LEONURINE; GLYCERIN; COMMIPHORA MYRRHA WHOLE; BORNEOL; OLIVE OIL; SOPHORA FLAVESCENS ROOT; CROCUS SATIVUS FLOWER; IMPATIENS BALSAMINA FLOWER; SMILACIN; PURSLANE; CYRTOMIUM FORTUNEI WHOLE; EUCALYPTUS SMITHII OIL; ALOE FEROX LEAF; STEPHANIA JAPONICA WHOLE; GLEDITSIA SINENSIS THORN; ISATIDINE

WARNINGS

If you experience any discomfort, please stop using and seek medical attention promptly

DOSAGE AND ADMINISTRATION

【 Instructions 】 Take an appropriate amount of this product and apply it to the surface of the skin.Once in the morning and once in the evening.

Keep out of reach of children

PURPOSE

This product is used for skin antibacterial purposes